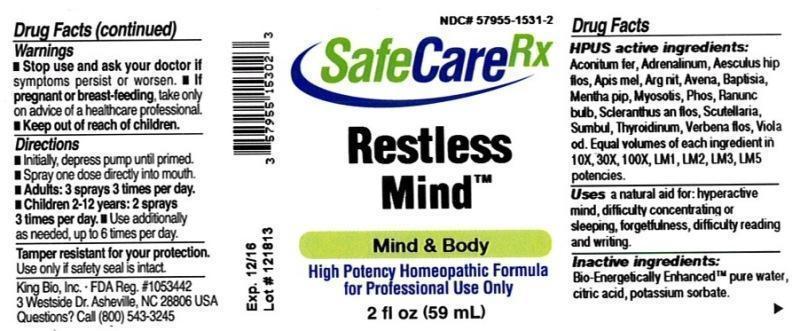 DRUG LABEL: Restless Mind
NDC: 57955-1531 | Form: LIQUID
Manufacturer: King Bio Inc.
Category: homeopathic | Type: HUMAN OTC DRUG LABEL
Date: 20131223

ACTIVE INGREDIENTS: ACONITUM FEROX ROOT 10 [hp_X]/59 mL; EPINEPHRINE 10 [hp_X]/59 mL; AESCULUS HIPPOCASTANUM FLOWER 10 [hp_X]/59 mL; APIS MELLIFERA 10 [hp_X]/59 mL; SILVER NITRATE 10 [hp_X]/59 mL; AVENA SATIVA FLOWERING TOP 10 [hp_X]/59 mL; BAPTISIA TINCTORIA ROOT 10 [hp_X]/59 mL; MENTHA PIPERITA 10 [hp_X]/59 mL; MYOSOTIS ARVENSIS 10 [hp_X]/59 mL; PHOSPHORUS 10 [hp_X]/59 mL; RANUNCULUS BULBOSUS 10 [hp_X]/59 mL; SCLERANTHUS ANNUUS FLOWERING TOP 10 [hp_X]/59 mL; SCUTELLARIA LATERIFLORA 10 [hp_X]/59 mL; FERULA SUMBUL ROOT 10 [hp_X]/59 mL; THYROID, UNSPECIFIED 10 [hp_X]/59 mL; VERBENA OFFICINALIS FLOWERING TOP 10 [hp_X]/59 mL; VIOLA ODORATA 10 [hp_X]/59 mL
INACTIVE INGREDIENTS: WATER; CITRIC ACID MONOHYDRATE; POTASSIUM SORBATE

Restless Mind

Drug Facts

____________________________________________________________________________________________________________________

HPUS active ingredients: Aconitum ferox, Adrenalinum, Aesculus hippocastanum, flos, Apis mellifica, Argentum nitricum, Avena sativa, Baptisia tinctor, Mentha piperita, Myosotis arvensis, Phosphorus, Ranunculus bulbosus, Scleranthus annuus, flos, Scutellaria lateriflora, Sumbul, Thyroidinum, Verbena officinalis, flos, Viola odorata. Equal volumes of each ingredient in 10X, 30X, 100X, LM1, LM2, LM3, LM5 potencies.

INDICATIONS AND USAGE

Uses a natural aid for: hyperactive mind, difficulty concentrating or sleeping, forgetfulness, difficulty reading and writing.

INACTIVE INGREDIENT

Inactive ingredients: Bio-Energetically Enhanced pure water, citric acid, potassium sorbate.

Warnings

- Stop use and ask your doctor if symptoms persist or worsen.
- If pregnant or breast-feeding, take only on advice of a healthcare professional.

- Keep out of reach of children.

Directions:

- Initially, depress pump until primed.
- Spray one dose directly into mouth.
- Adults: 3 sprays 3 times per day.
- Children 2-12 years: 2 sprays 3 times per day.
- Use additionally as needed, up to 6 times per day.

OTHER SAFETY INFORMATION

Tamper resistant for your protection. Use only if safety seal is intact.

PURPOSE

Uses a natural aid for:

- hyperactive mind
- difficulty concentrating or sleeping
- forgetfulness
- difficulty reading and writing.